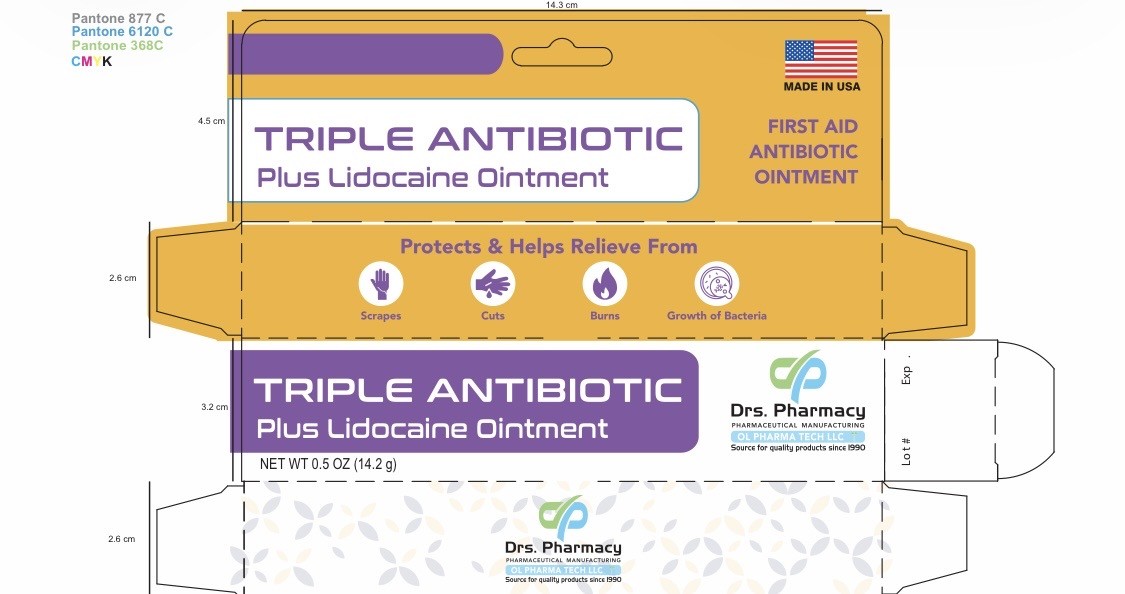 DRUG LABEL: Drs. pharmacy triple antibiotic plus lidocaine
NDC: 80489-912 | Form: OINTMENT
Manufacturer: OL PHARMA TECH, LLC
Category: otc | Type: HUMAN OTC DRUG LABEL
Date: 20260130

ACTIVE INGREDIENTS: NEOMYCIN SULFATE 3.5 mg/1 g; BACITRACIN ZINC 500 [USP'U]/1 g; POLYMYXIN B SULFATE 10000 [USP'U]/1 g; LIDOCAINE 40 mg/1 g
INACTIVE INGREDIENTS: PETROLATUM

Active Ingredients

- Bacitracin Zinc 400 units
- Neomycin Sulfate 3.5mg
- Polymyxin B Sulfate 5,000 units
- Lidocaine 40 mg

Purpose

- First aid antibiotic

Uses

First aid to help prevent infection and temporary relief of pain in minor:

- cuts
- scrapes
- burns

Warnings

For external use only

Ask a doctor before use if you have

- serious burns
- deep or puncture wounds
- animal bites

Stop use and ask a doctor if

- if you need to use longer than 1 week
- condition persists or gets worse
- symptoms persist for more than 1 week, or clear up and occur again within a few days.
- rash or other allergic reaction develops

- do not use in the eyes
- do not apply over large areas of the body
- if you are allergic to any of the ingredients
- longer than one week unless directed by your doctor
- in large quantities, particularly over raw surfaces or blistered areas

keep out of the reach of children

If swallowed, get medical help or contact a Poison Control Center right away

Directions

adults and children 2 years of age and older:

- clean the affected area
- apply a small amount of this product (an amount equal tot the surface area of the tip of a finer) on the area 1 to 3 times daily
- may be covered with a sterile bandage

children under 2 years of age: ask a doctor

OTHER SAFETY INFORMATION

- store at room temperature(68 to 77 F)

Inactive ingredient

Petrolatum

Questions

Call: 248 325 4231